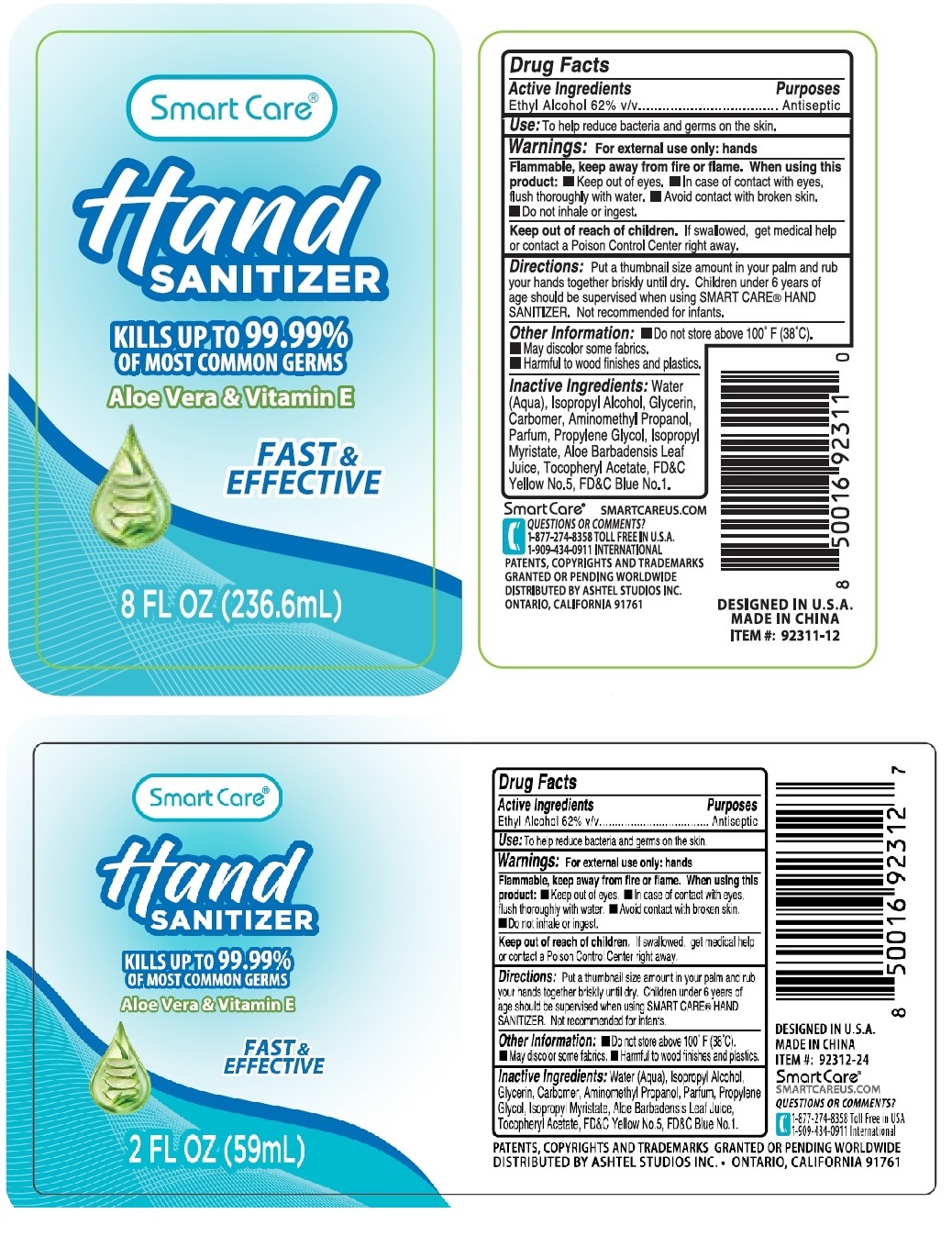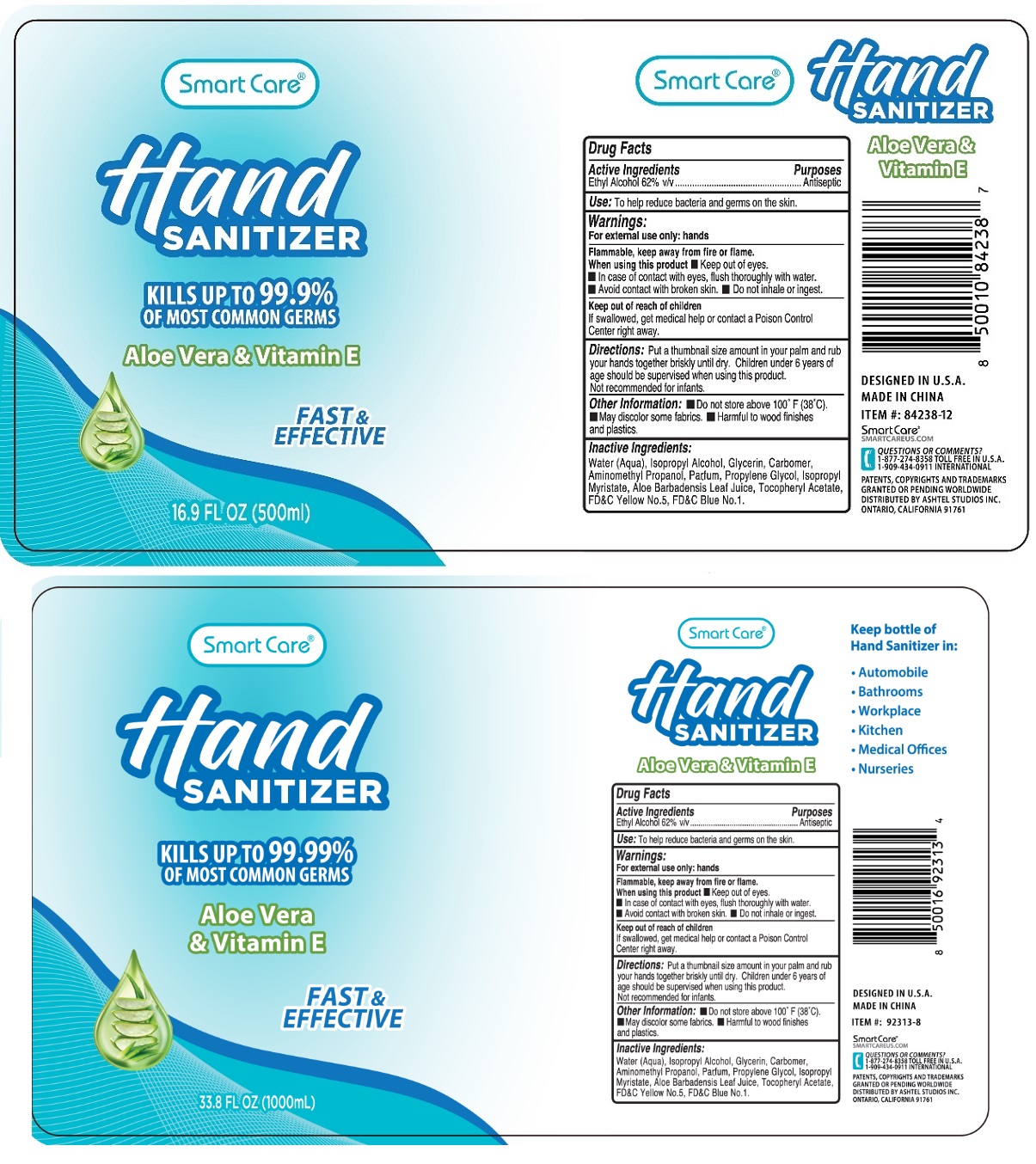 DRUG LABEL: Smart Care HAND SANITIZER
NDC: 54860-215 | Form: GEL
Manufacturer: Shenzhen Lantern Science Co., ltd.
Category: otc | Type: HUMAN OTC DRUG LABEL
Date: 20230512

ACTIVE INGREDIENTS: ALCOHOL 62 mL/100 mL
INACTIVE INGREDIENTS: WATER; ISOPROPYL ALCOHOL; GLYCERIN; CARBOMER HOMOPOLYMER, UNSPECIFIED TYPE; AMINOMETHYLPROPANOL; PROPYLENE GLYCOL; ISOPROPYL MYRISTATE; ALOE VERA LEAF; .ALPHA.-TOCOPHEROL ACETATE; FD&C YELLOW NO. 5; FD&C BLUE NO. 1

Smart Care® Hand SANITIZER

Active Ingredients

Ethyl Alcohol 62% v/v

Purposes

Antiseptic

Use:

To help reduce bacteria and germs on the skin.

Warnings:

For external use only: hands

Flammable. Keep away from fire or flame.

When using this product

• Keep out of eyes.

• In case of contact with eyes, flush thoroughly with water.

• Avoid contact with broken skin.

• Do not inhale or ingest.

Keep out of reach of children

If swallowed, get medical help or contact a Poison Control Center right away.

Directions:

Put a thumbnail size amount in your palm and rub your hands together briskly until dry. Children under 6 years of age should be supervised when using SMART CARE® HAND SANITIZER. Not recommended for infants.

Other Information:

• Do not store above 100° F (38°C)

• May discolor some fabrics.

• Harmful to wood finishes and plastics.

Inactive Ingredients:

Water (Aqua), Isopropyl Alcohol, Glycerin, Carbomer, Aminomethyl Propanol, Parfum, Propylene Glycol, Isopropyl Myristate, Aloe Barbadensis Leaf Juice, Tocopheryl Acetate, FD&C Yellow No. 5, FD&C Blue No. 1.

KILLS UP TO 99.99% OF MOST COMMON GERMS

Aloe Vera & Vitamin E

FAST & EFFECTIVE

Keep bottle of Hand Sanitizer in:

- Automobile
- Bathrooms
- Workplace
- Kitchen
- Medical Offices
- Nurseries

SMARTCAREUS.COM

QUESTIONS OR COMMENTS?

1-877-274-8358 TOLL FREE IN U.S.A.

1-909-434-0911 INTERNATIONAL

PATENTS, COPYRIGHTS AND TRADEMARKS GRANTED OR PENDING WORLDWIDE

DISTRIBUTED BY ASHTEL STUDIOS INC. ONTARIO, CALIFORNIA 91761

DESIGNED IN U.S.A.

MADE IN CHINA